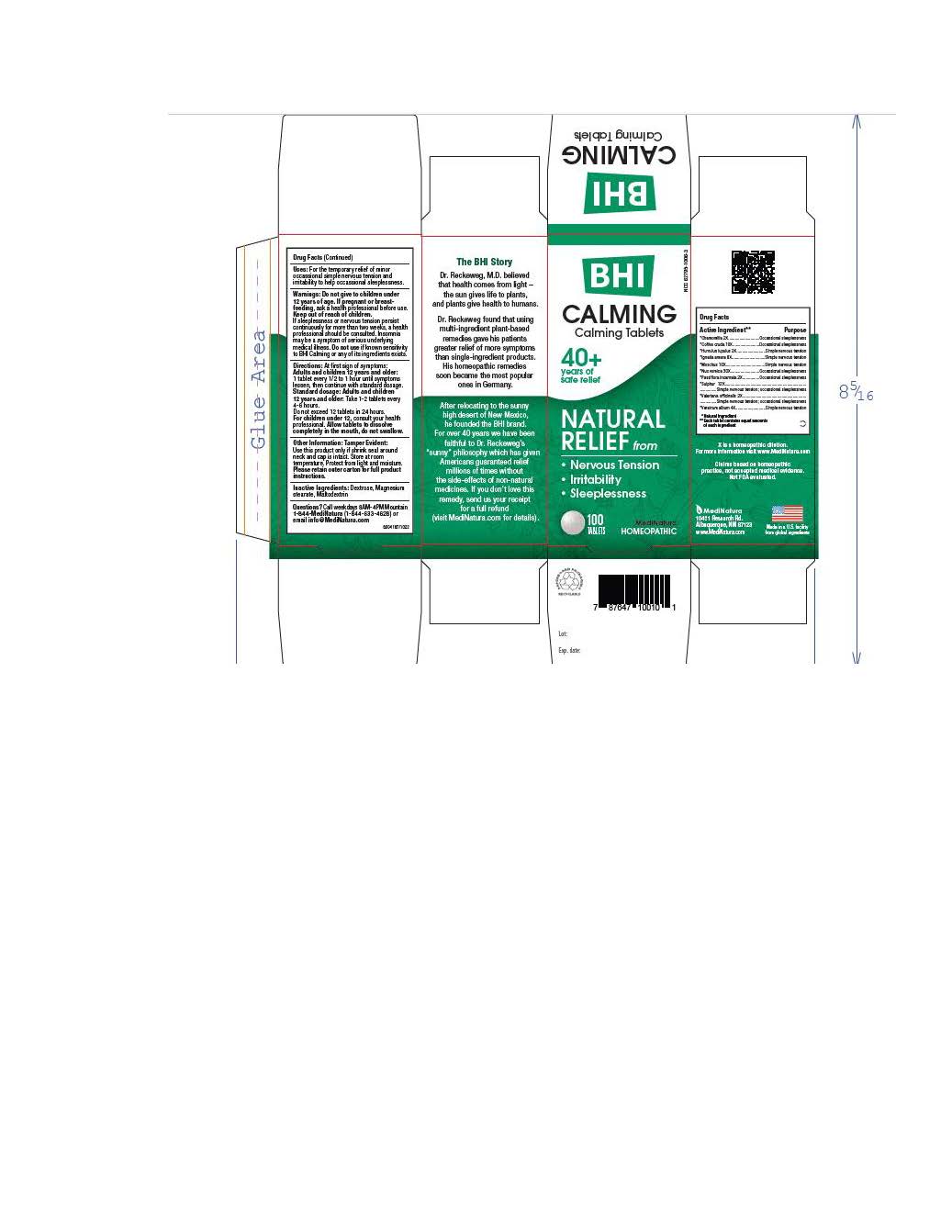 DRUG LABEL: BHI Calming
NDC: 62795-1006 | Form: TABLET
Manufacturer: MediNatura Inc
Category: homeopathic | Type: HUMAN OTC DRUG LABEL
Date: 20230802

ACTIVE INGREDIENTS: MATRICARIA RECUTITA 2 [hp_X]/1 1; ARABICA COFFEE BEAN 10 [hp_X]/1 1; HOPS 2 [hp_X]/1 1; STRYCHNOS IGNATII SEED 8 [hp_X]/1 1; MOSCHUS MOSCHIFERUS MUSK SAC RESIN 10 [hp_X]/1 1; STRYCHNOS NUX-VOMICA SEED 30 [hp_X]/1 1; PASSIFLORA INCARNATA FLOWERING TOP 2 [hp_X]/1 1; SULFUR 12 [hp_X]/1 1; VALERIAN 2 [hp_X]/1 1; VERATRUM ALBUM ROOT 4 [hp_X]/1 1
INACTIVE INGREDIENTS: LACTOSE; MAGNESIUM STEARATE; MALTODEXTRIN; DEXTROSE

BHI Calming Tablet

ACTIVE INGREDIENT

Each tablet contains: *Chamomilla 2X, *Coffea cruda 10X, *Humulus lupulus 2X, *Ignatia amara 8X, *Moschus 10X, *Nux vomica 30X, *Passiflora incarnata 2X, *Sulphur 12X, *Valeriana officinalis 2X, *Veratrum album 4X 30 mg each.

*Natural Ingredients

INACTIVE INGREDIENTS

Inactive Ingredients: **Dextrose, ** Lactose, Magnesium Stearate, **Maltodextrin
**contains one or more of these ingredients.

PURPOSE

Calming Tablets

Relieves:

• Nervous Tension

• Irritability

• Sleeplessness

USES

For the temporary relief of minor occassional simple nervous tension and irritability to help occassional sleeplessness

DIRECTIONS

At first sign of symptoms: Adults and children 12 years and older:

1 tablet every 1/2 to 1 hour until symptoms lessen, then continue with standard dosage.

Standard dosage: Adults and children 12 years and older: Take 1-2 tablets every 4 to 6 hours. Do not exceed 12 tablets in 24 hours.

For children under 12, consult your health professional.

Allow tablets to dissolve completely in the mouth, do not swallow.

WARNINGS

Do not give to children under 12 years of age. If pregnant or breast-feeding, ask a health professional before use. Keep out of reach of children. If sleeplessness or nervous tension persist continuously for more than two weeks, a health professional should be consulted. Insomnia may be a symptom of serious underlying medical illness. Do not use if known sensitivity to BHI Calming or any of its ingredients exists

PACKAGE LABEL

Add image transcription here...